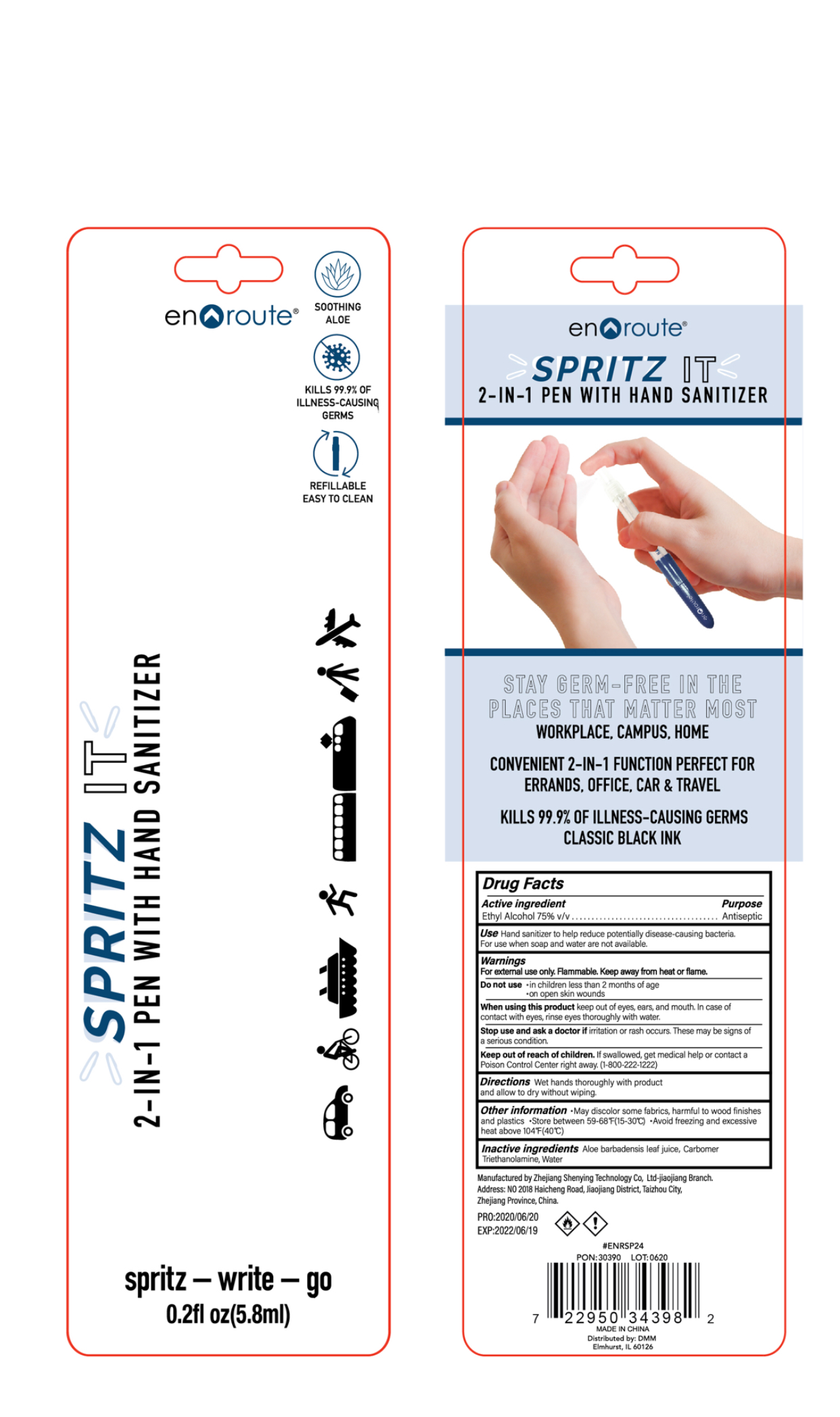 DRUG LABEL: SPRITZ IT 2 in 1 Pen with Hand Sanitizer
NDC: 75112-008 | Form: SPRAY
Manufacturer: Zhejiang Shenying Technology Co., Ltd. Jiaojiang Branch
Category: otc | Type: HUMAN OTC DRUG LABEL
Date: 20200815

ACTIVE INGREDIENTS: ALCOHOL 75 mL/100 mL
INACTIVE INGREDIENTS: WATER; CARBOMER 940; TROLAMINE; ALOE VERA LEAF

Active Ingredient(s)

Ethyl Alcohol 75%

Purpose

Antiseptic

Use

Hand sanitizer to help reduce potentially disease causing bacteria

Warnings

For external use only

Flammable. Keep away from heat or flame

When using this product keep out of eyes, ears, and mouth. In case of eye contact with eyes, rinse eyes thoroughly with water.

Stop use and ask a doctor if irritation or rash occurs. This may be signs of serious condition

Do not use

on children less than 2 months of age

on open skin wounds

Keep out of reach of children. If swallowed, get medical help or contact a Poison Control Center right away.

Directions

Wet hands thoroughyl with product and allow to dry withour wiping

Other information

May discolor some fabrics, harmful to wood finishes and plastics

Store between 59-68 F (15-30C)

Avoid freezing and excessive heat above 104F (40C)

Inactive ingredients

Water, aloe barbadensis leaf jiuce, carbomer, triethanolamine